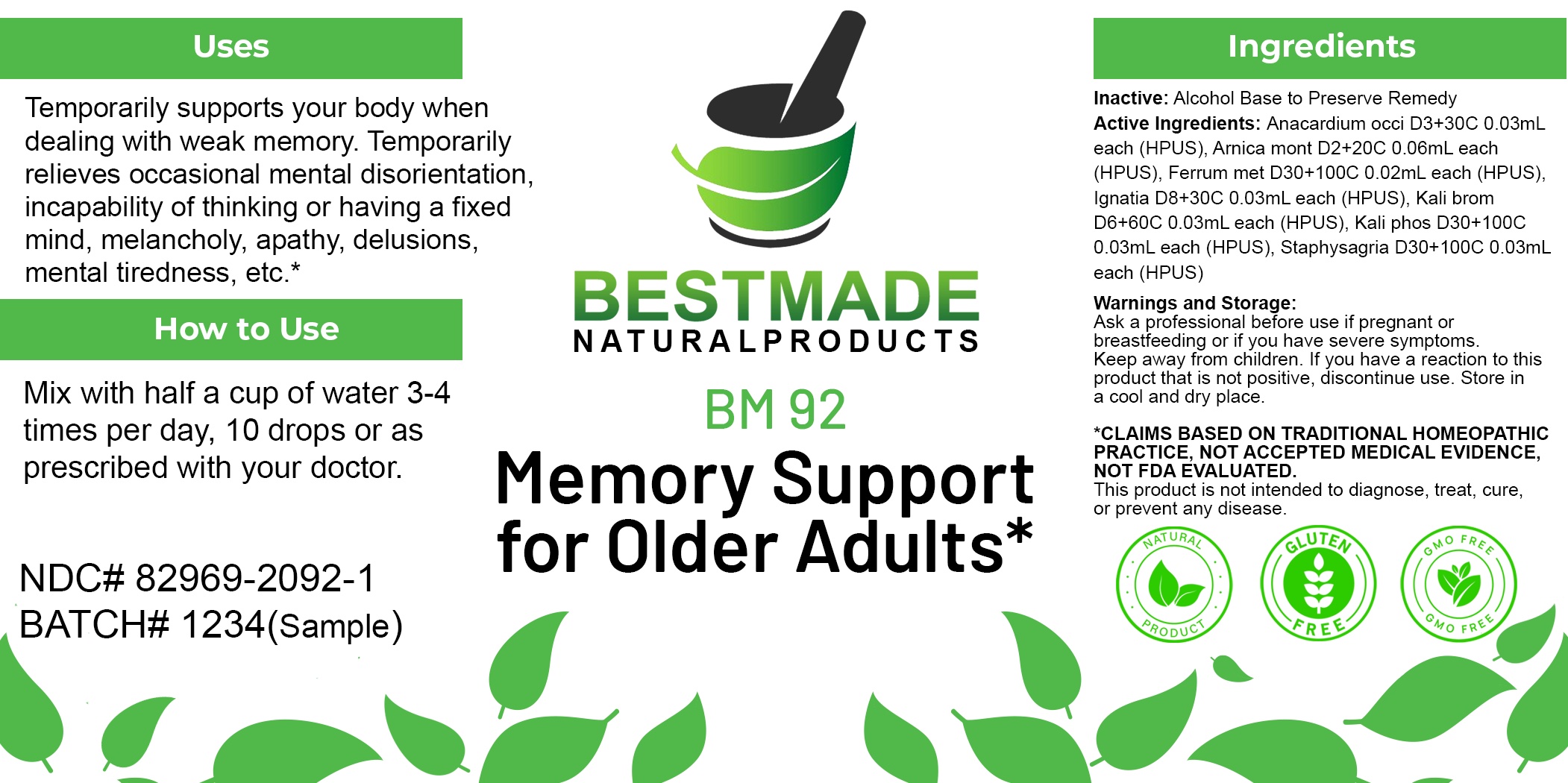 DRUG LABEL: Bestmade Natural Products BM92
NDC: 82969-2092 | Form: LIQUID
Manufacturer: Bestmade Natural Products
Category: homeopathic | Type: HUMAN OTC DRUG LABEL
Date: 20250203

ACTIVE INGREDIENTS: POTASSIUM BROMIDE 30 [hp_C]/30 [hp_C]; ANACARDIUM OCCIDENTALE FRUIT 30 [hp_C]/30 [hp_C]; STRYCHNOS IGNATII SEED 30 [hp_C]/30 [hp_C]; POTASSIUM PHOSPHATE 30 [hp_C]/30 [hp_C]; IRON 30 [hp_C]/30 [hp_C]; ARNICA MONTANA 30 [hp_C]/30 [hp_C]; DELPHINIUM STAPHISAGRIA SEED 30 [hp_C]/30 [hp_C]
INACTIVE INGREDIENTS: ALCOHOL 30 [hp_C]/30 [hp_C]

BM92

DOSAGE AND ADMINISTRATION

How to Use

Mix with half a cup of water 3-4 times per day, 10 drops or as prescribed with your doctor.

INACTIVE INGREDIENT

Ingredients

Inactive: Alcohol Base to Preserve Remedy

ACTIVE INGREDIENT

Active Ingredients: Anacardium occi D3+30C 0.03mL each (HPUS), Arnica mont D2+20C 0.06mL each (HPUS), Ferrum met D30+100C 0.02mL each (HPUS), Ignatia D8+30C 0.03mL each (HPUS), Kali brom D6+60C 0.03mL each (HPUS), Kali phos D30+100C 0.03mL each (HPUS), Staphysagria D30+100C 0.03mL each (HPUS).

Uses

Temporarily supports your body when dealing with weak memory. Temporarily relieves occasional mental disorientation, incapability of thinking or having a fixed mind, melancholy, apathy, delusions, mental tiredness, etc.*

*CLAIMS BASED ON TRADITIONAL HOMEOPATHIC PRACTICE, NOT ACCEPTED MEDICAL EVIDENCE, NOT FDA EVALUATED.

This product is not intended to diagnose, treat, cure, or prevent any disease.

Uses

Temporarily supports your body when dealing with weak memory. Temporarily relieves occasional mental disorientation, incapability of thinking or having a fixed mind, melancholy, apathy, delusions, mental tiredness, etc.*

*CLAIMS BASED ON TRADITIONAL HOMEOPATHIC PRACTICE, NOT ACCEPTED MEDICAL EVIDENCE, NOT FDA EVALUATED.

This product is not intended to diagnose, treat, cure, or prevent any disease.

KEEP OUT OF REACH OF CHILDREN

Warnings and Storage:

Ask a professional before use if pregnant or breastfeeding or if you have severe symptoms. Keep away from children. If you have a reaction to this product that is not positive, discontinue use. Store in a cool and dry place.

Warnings and Storage:

Ask a professional before use if pregnant or breastfeeding or if you have severe symptoms. Keep away from children. If you have a reaction to this product that is not positive, discontinue use. Store in a cool and dry place.

*CLAIMS BASED ON TRADITIONAL HOMEOPATHIC PRACTICE, NOT ACCEPTED MEDICAL EVIDENCE, NOT FDA EVALUATED.

This product is not intended to diagnose, treat, cure, or prevent any disease.

Entire package label